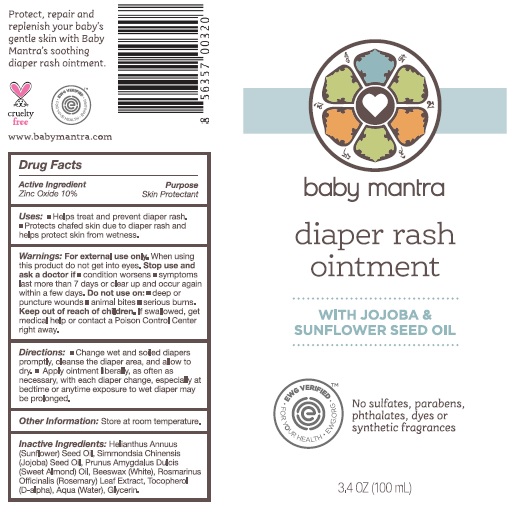 DRUG LABEL: Diaper Cream
NDC: 62932-175 | Form: OINTMENT
Manufacturer: Private Label Select Ltd CO
Category: otc | Type: HUMAN OTC DRUG LABEL
Date: 20181116

ACTIVE INGREDIENTS: ZINC OXIDE 20 g/100 g
INACTIVE INGREDIENTS: HELIANTHUS ANNUUS SEED WAX; SIMMONDSIA CHINENSIS SEED WAX; ALMOND OIL; TOCOPHEROL; WATER; WHITE WAX; GLYCERIN; ROSEMARY

baby mantra Diaper Rash Ointment